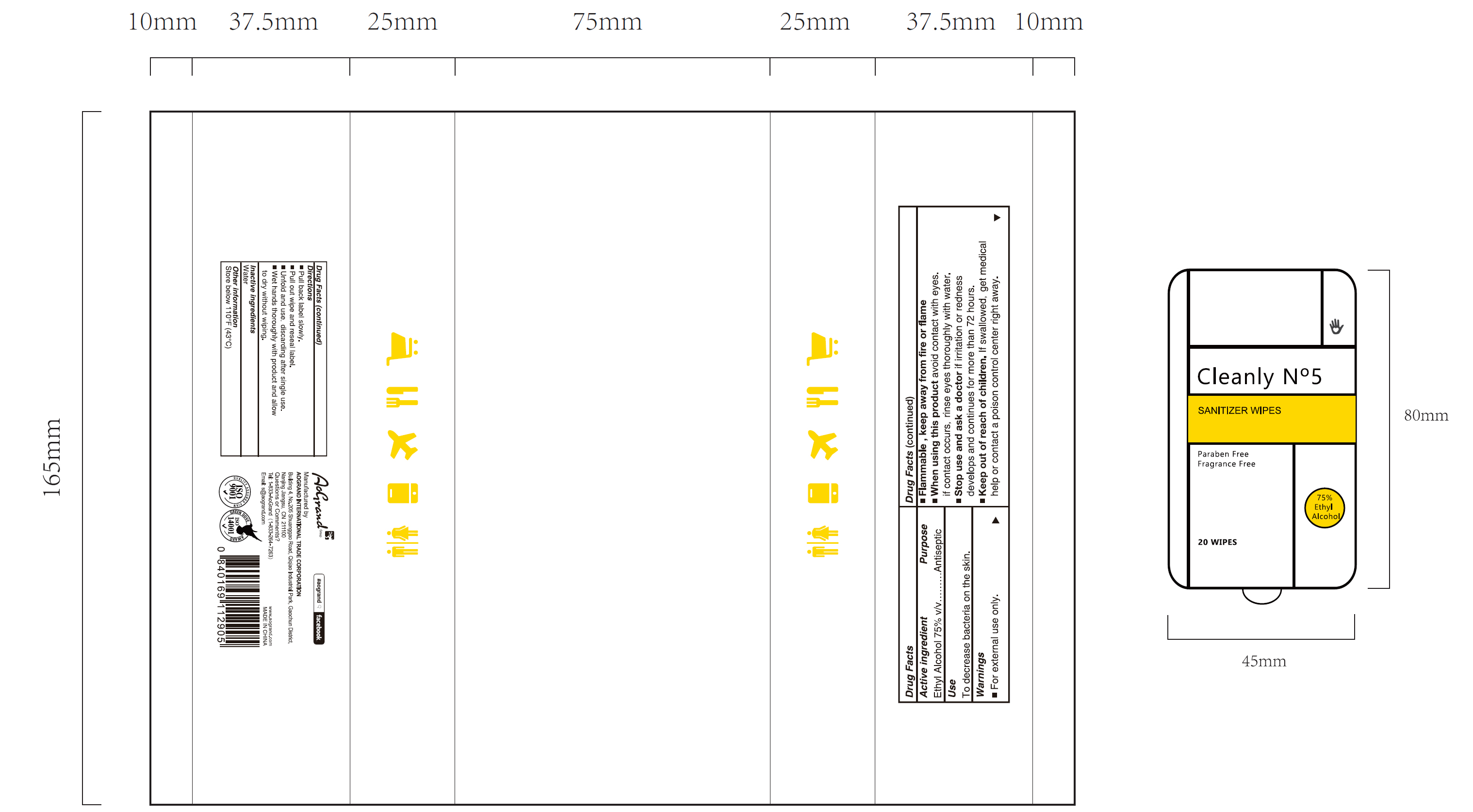 DRUG LABEL: Cleanly N5 Sanitizer wipes 20pcs
NDC: 74621-021 | Form: CLOTH
Manufacturer: Aogrand International Trade Corporation
Category: otc | Type: HUMAN OTC DRUG LABEL
Date: 20230211

ACTIVE INGREDIENTS: ALCOHOL 75 mL/100 g
INACTIVE INGREDIENTS: WATER

Cleanly N°5 Sanitizer wipes 20pcs

Active Ingredient

Ethyl Alcohol 75% v/v. Purpose: Antiseptic

Purpose

Antiseptic

Uses

To decrease bacteria on the skin.

Warnings

For external use only.

Flammable. Keep away from fire or flame.

When using this product

avoid contact with eyes. If contact occurs, rinses eyes thoroughly with water.

Stop use and ask a doctor if

irritation or redness develops and continues for more than 72 hours.

Keep out of reach of children.

If swallowed, get medical help or contact a poison control center right away.

Directions

- Pull back label slowly.
- Pull out wipe and reseal label.
- Unfold and use, discarding after single use.
- Wet hands thoroughly with product and allow to dry without wiping.

Inactive ingredients

Water

Other information

- Store below 110F (43C)

Package Label - Principal Display Panel

20PCS NDC: 74621-021-01

Cleanly N°5

Sanitizer wipes

Paraben Free

Fragrance Free

75% Ethyl Alcohol

20 WIPES